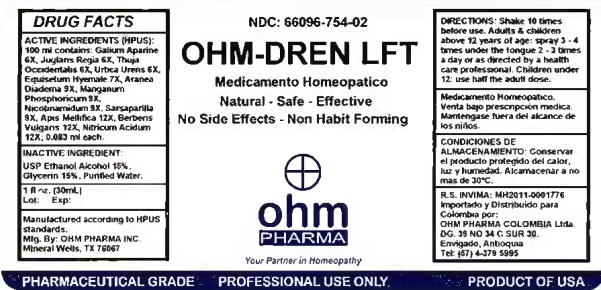 DRUG LABEL: OHM-DREN LFT
NDC: 66096-754 | Form: SPRAY
Manufacturer: OHM PHARMA INC.
Category: homeopathic | Type: HUMAN PRESCRIPTION DRUG LABEL
Date: 20210111

ACTIVE INGREDIENTS: APIS MELLIFERA 12 [hp_X]/30 mL; ARANEUS DIADEMATUS 9 [hp_X]/30 mL; BERBERIS VULGARIS ROOT BARK 12 [hp_X]/30 mL; EQUISETUM HYEMALE 7 [hp_X]/30 mL; GALIUM APARINE 6 [hp_X]/30 mL; JUGLANS REGIA WHOLE 6 [hp_X]/30 mL; MANGANESE PHOSPHATE, DIBASIC 9 [hp_X]/30 mL; NIACINAMIDE 9 [hp_X]/30 mL; NITRIC ACID 12 [hp_X]/30 mL; SARSAPARILLA 9 [hp_X]/30 mL; THUJA OCCIDENTALIS LEAFY TWIG 6 [hp_X]/30 mL; URTICA URENS 6 [hp_X]/30 mL
INACTIVE INGREDIENTS: ALCOHOL; GLYCERIN; WATER

OHM-DREN LFT

ACTIVE INGREDIENT

ACTIVE INGREDIENTS (HPUS): 100 ml contains: Galium Aparine 6X, Juglans Regia 6X, Thuja Occidentalis 6X, Urtica Urens 6X, Equisetum Hyemale 7X, Aranea Diadema 9X, Manganum Phosphoricum 9X, Nicotinamidum 9X, Sarsaparilla 9X, Apis Mellifica 12X, Berberis Vulgaris 12X, Nitricum Acidum 12X; 0.083 ml each.

INDICATIONS AND USAGE

USES: Temporarily relieves slow lymphatic drainage. Assists in removing toxins and improves metabolism.**

WARNINGS

Medicamento Homeopatico.

Venta bajo prescripsion medica.

Mantengase fuera del alcance de

los niños.

KEEP OUT OF REACH OF CHILDREN

Mantengase fuera del alcance de los niños.

DOSAGE AND ADMINISTRATION

Directions: Shake 10 times before use. Adults & children above 12 years of age: spray 3 - 4 times under the tongue 2-3 times a day or as directed by a health care professional. Children under 12: use half the adult dose.

OTHER SAFETY INFORMATION

CONDICIONES DE ALMACENAMIENTO: Conservar el producto protegido del calor, luz y humedad. Alcamacenar a no mas de 30°C.

INACTIVE INGREDIENT:

USP Ethanol Alcohol 15%,

Glycerin 15%, Purified Water.

QUESTIONS

Manufactured according to HPUS

standards.

Mfg. By: OHM PHARMA INC.

Mineral Wells, TX 76067

R.S. INVIMA: MH2011-0001776

Importado y Distribuido para

Colombia por:

OHM PHARMA COLOMBIA Ltda.

DG. 39 NO C SUR 30

Envigado, Antioquia

Tel: (57) 4-379 5995

PACKAGE LABEL

NDC: 66096-754-02

OHM-DREN LFT

Medicamento Homeopatico

Natural - Safe - Effective

No Side Effects - Non Habit Forming

PURPOSE

USES: Temporarily relieves slow lymphatic drainage. Assists in removing toxins and improves metabolism.**